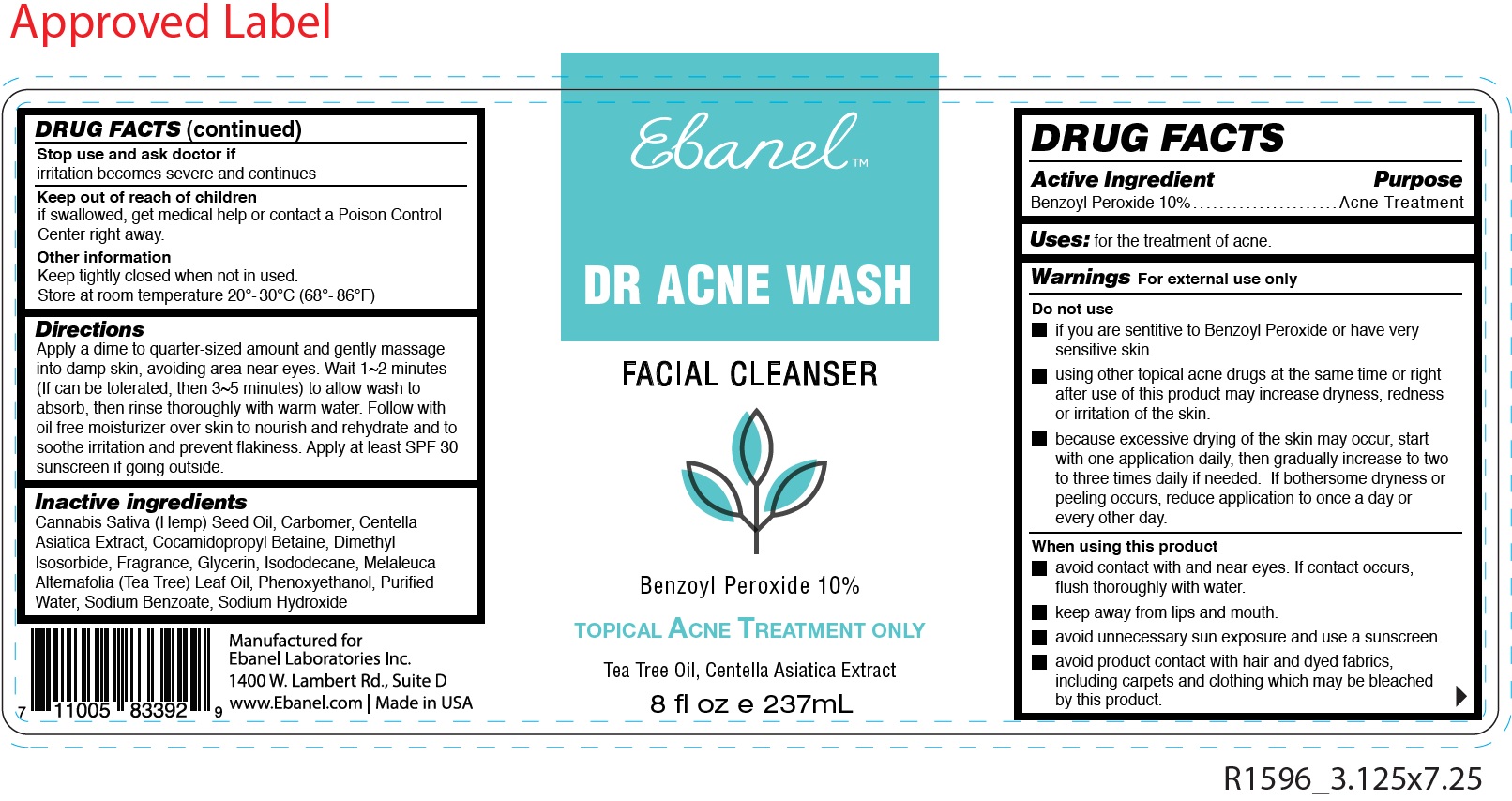 DRUG LABEL: Dr Acne Wash Facial Cleanser
NDC: 63742-020 | Form: CREAM
Manufacturer: Clinical Resolution Laboratory, Inc.
Category: otc | Type: HUMAN OTC DRUG LABEL
Date: 20231226

ACTIVE INGREDIENTS: BENZOYL PEROXIDE 100 mg/1 mL
INACTIVE INGREDIENTS: CANNABIS SATIVA SEED OIL; CARBOXYPOLYMETHYLENE; CENTELLA ASIATICA; COCAMIDOPROPYL BETAINE; DIMETHYL ISOSORBIDE; GLYCERIN; ISODODECANE; MELALEUCA ALTERNIFOLIA LEAF; PHENOXYETHANOL; WATER; SODIUM BENZOATE; SODIUM HYDROXIDE

Dr Acne Wash Facial Cleanser

Active Ingredient

Benzoyl Peroxide 10%

Purpose

Acne Treatment

Uses:

for the treatment of acne.

Warnings

For external use only

Do not use

- if you are sentitive to Benzoyl Peroxide or have very sensitive skin.
- using other topical acne drugs at the same time or right after use of this product may increase dryness, redness or irritation of the skin.
- because excessive drying of the skin may occur, start with one application daily, then gradually increase to two to three times daily if needed. If bothersome dryness or peeling occurs, reduce application to once a day or every other day.

When using this product

- avoid contact with and near eyes. If contact occurs, flush thoroughly with water.
- keep away from lips and mouth.
- avoid unnecessary sun exposure and use a sunscreen.
- avoid product contact with hair and dyed fabrics, including carpets and clothing which may be bleached by this product.

Stop use and ask doctor if

irritation becomes severe and continues

Keep out of reach of children

if swallowed, get medical help or contact a Poison Control Center right away.

Other information

Keep tightly closed when not in used. Store at room temperature 20°- 30°C (68°- 86°F)

Directions

Apply a dime to quarter-sized amount and gently massage into damp skin, avoiding area near eyes. Wait 1~2 minutes (If can be tolerated, then 3~5 minutes) to allow wash to absorb, then rinse thoroughly with warm water. Follow with oil free moisturizer over skin to nourish and rehydrate and to soothe irritation and prevent flakiness. Apply at least SPF 30 sunscreen if going outside.

Inactive ingredients

Cannabis Sativa (Hemp) Seed Oil, Carbomer, Centella Asiatica Extract, Cocamidopropyl Betaine, Dimethyl Isosorbide, Fragrance, Glycerin, Isododecane, Melaleuca Alternafolia (Tea Tree) Leaf Oil, Phenoxyethanol, Purified Water, Sodium Benzoate, Sodium Hydroxide